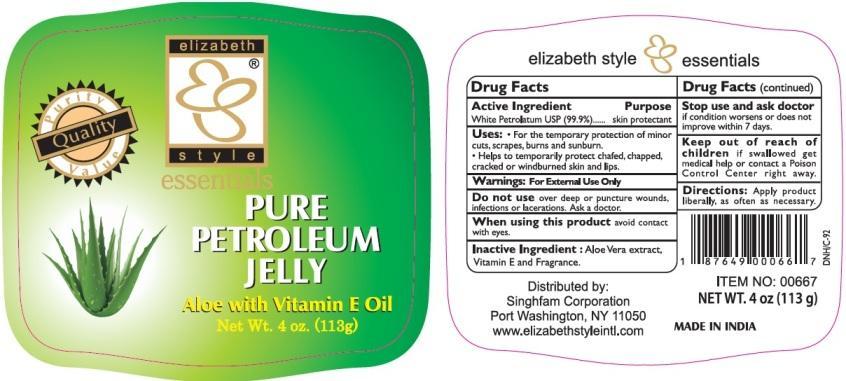 DRUG LABEL: Pure Petroleum
NDC: 52920-127 | Form: JELLY
Manufacturer: Singhfam Corporation
Category: otc | Type: HUMAN OTC DRUG LABEL
Date: 20221121

ACTIVE INGREDIENTS: PETROLATUM 99.9 g/100 g
INACTIVE INGREDIENTS: ALOE VERA LEAF; .ALPHA.-TOCOPHEROL

Pure Petroleum Aloe with Vitamin E Oil Jelly

Active Ingredient

White Petrolatum USP (99.9 %)

Purpose

Skin Protectant

Uses

For the temporary protection of minor cuts, scrapes, burns and sunburn.

- Helps to temporarily protect chafed, chapped, cracked or windburned skin and lips.

Warnings

For External Use Only.

Do not use over deep or puncture wounds, infections or lacerations. Ask a doctor.

When using this product avoid contact with eyes.

Stop use and ask doctor if conditon worsens or does not improve within 7 days.

Keep out of reach of children if swallowed get medical help or contact a Poison Control Center right away.

Directions

Apply product liberally, as often as necessary.

Inactive Ingredients

Aloe Vera Extract, Vitamin E and Fragrance

PACKAGE LABEL

PRINCIPAL DISPLAY PANEL

Pure Petroleum Aloe with Vitamin E Oil Jelly

Net Wt. 4 oz. (113g)